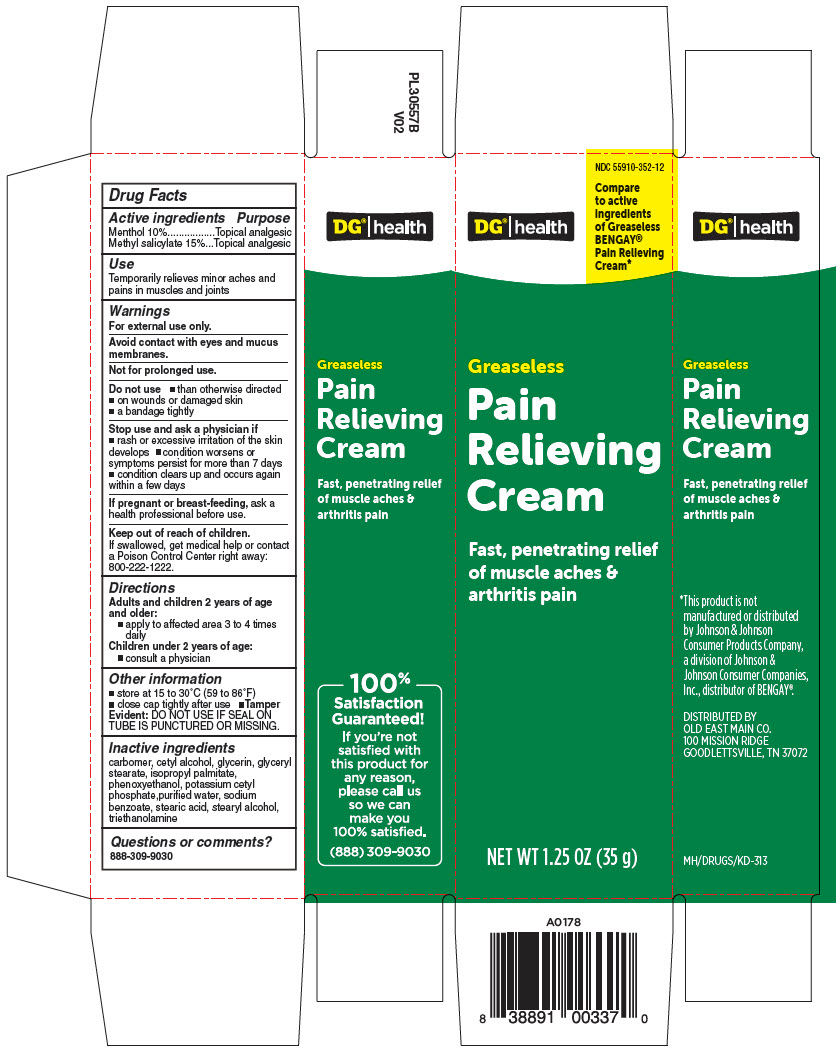 DRUG LABEL: DGH GREASELESS MUSCLE RUB 
NDC: 55910-352 | Form: CREAM
Manufacturer: DOLLAR GENERAL
Category: otc | Type: HUMAN OTC DRUG LABEL
Date: 20241217

ACTIVE INGREDIENTS: MENTHOL, UNSPECIFIED FORM 0.1 mg/1 g; METHYL SALICYLATE 0.15 mg/1 g
INACTIVE INGREDIENTS: CARBOMER HOMOPOLYMER, UNSPECIFIED TYPE; CETYL ALCOHOL; GLYCERIN; GLYCERYL MONOSTEARATE; ISOPROPYL PALMITATE; PHENOXYETHANOL; POTASSIUM CETYL PHOSPHATE; WATER; SODIUM BENZOATE; STEARIC ACID; STEARYL ALCOHOL; TROLAMINE

DGH® GREASELESS MUSCLE RUB
TOPICAL ANALGESIC

Drug Facts

ACTIVE INGREDIENT

Active ingredients | Purpose
Menthol 10% | Topical analgesic
Methyl salicylate 15% | Topical analgesic

Use

Temporarily relieves minor aches and pains in muscles and joints

Warnings

For external use only.

Avoid contact with eyes and mucus membranes.

Not for prolonged use.

Do not use

- than otherwise directed
- on wounds or damaged skin
- a bandage tightly

Stop use and ask a physician if

- rash or excessive irritation of the skin develops
- condition worsens or symptoms persist for more than 7 days
- condition clears up and occurs again within a few days

PREGNANCY OR BREAST FEEDING

If pregnant or breast-feeding, ask a health professional before use.

Keep out of reach of children.

If swallowed, get medical help or contact a Poison Control Center right away:

800-222-1222.

Directions

Adults and children 2 years of age and older:

- apply to affected area 3 to 4 times daily

Children under 2 years of age:

- consult a physician

Other information

- store at 15 to 30°C (59 to 86°F)
- close cap tightly after use
- Tamper Evident: DO NOT USE IF SEAL ON TUBE IS PUNCTURED OR MISSING.

Inactive ingredients

carbomer, cetyl alcohol, glycerin, glyceryl stearate, isopropyl palmitate, phenoxyethanol, potassium cetyl phosphate,purified water, sodium benzoate, stearic acid, stearyl alcohol, triethanolamine

Questions or comments?

888-309-9030

DISTRIBUTED BY
OLD EAST MAIN CO.
100 MISSION RIDGE
GOODLETTSVILLE, TN 37072

PRINCIPAL DISPLAY PANEL - 35 g Tube Carton

NDC 55910-352-12

Compare
to active
ingredients
of Greaseless
BENGAY®
Pain Relieving
Cream*

DG®|health

Greaseless

Pain
Relieving
Cream

Fast, penetrating relief
of muscle aches &
arthritis pain

NET WT 1.25 OZ (35 g)